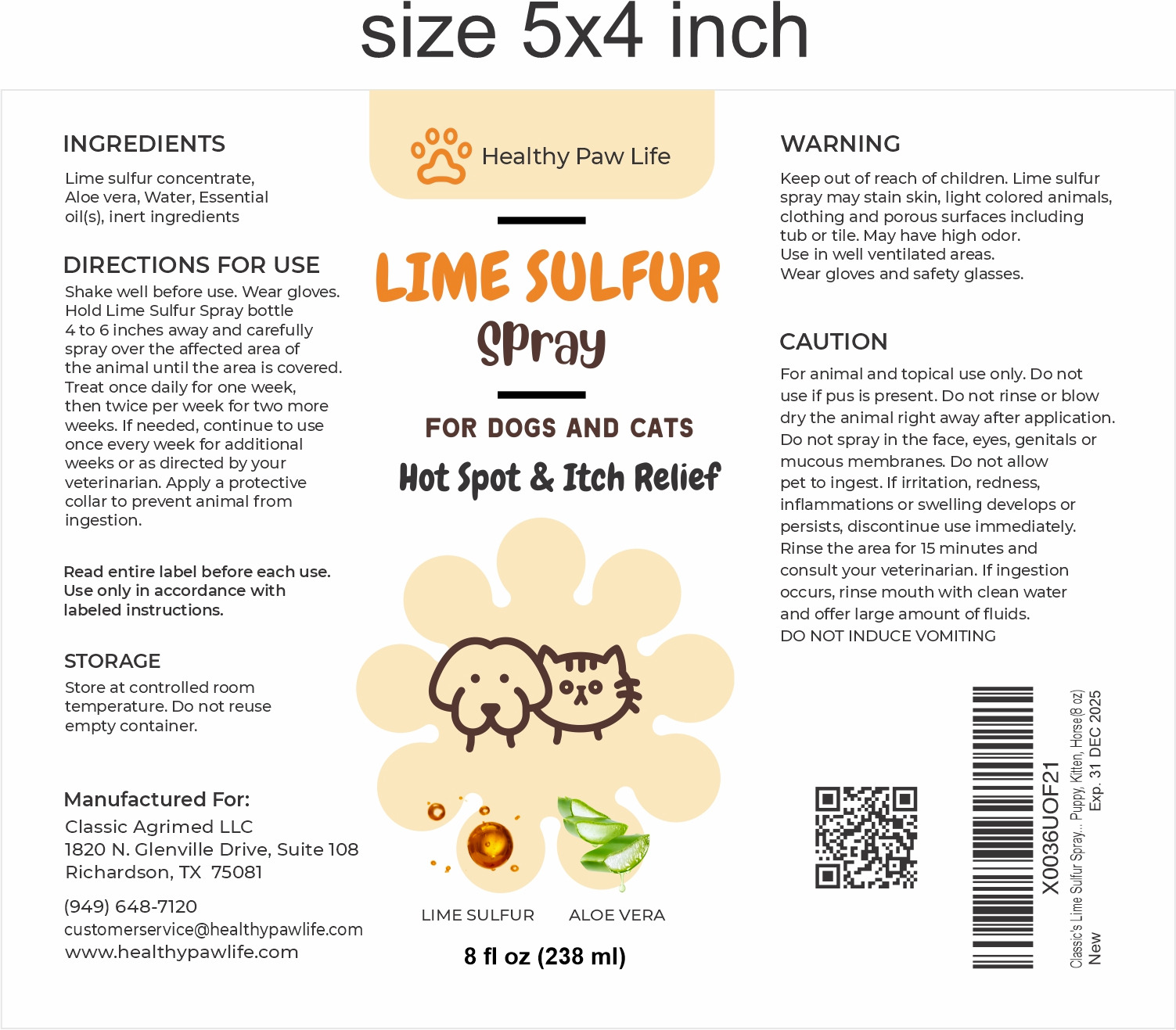 DRUG LABEL: CLASSIC LIME SULFUR SP
NDC: 86130-200 | Form: LIQUID
Manufacturer: CLASSIC AGRIMED LLC
Category: animal | Type: OTC ANIMAL DRUG LABEL
Date: 20231112

ACTIVE INGREDIENTS: CALCIUM POLYSULFIDE 1.5 g/100 mL
INACTIVE INGREDIENTS: WATER; ALOE

Ingredients:
Lime Sulfur Concentrate, Aloe Vera, Water, Essential oil(s), Other inert ingredients

Description:
Lime Sulfur Spray for Hot Spot & Itch Relief for Dogs and Cats.

Directions For Use:
Shake well before use. Wear gloves. Hold Lime Sulfur Spray bottle 4 to 6 inches away and carefully spray over the affected area of the animal until the area is covered. Treat once daily for one week, then twice per week for two more weeks. If needed, continue to use once every week for additional weeks or as directed by your veterinarian. Apply a protective collar to prevent animal from ingestion.

Read entire label before each use. Use only in accordance with labeled instructions.

Storage:
Store at controlled room temperature. Do not reuse empty container.

Warning:Keep out of reach of children. Lime sulfur spray may stain skin, light colored animals, clothing and porous surfaces including tub or tile. May have high odor. Use in well ventilated areas.Wear gloves and safety glasses.

Caution:

For animal and topical use only. Do not use if pus is present. Do not rinse or blow dry the animal right away after application.
Do not spray in the face, eyes, genitals or mucous membranes. Do not allow pet to ingest. If irritation, redness, inflammations or swelling develops or persists, discontinue use immediately. Rinse the area for 15 minutes and consult your veterinarian. If ingestion occurs, rinse mouth with clean water and offer large amount of fluids.
DO NOT INDUCE VOMITING